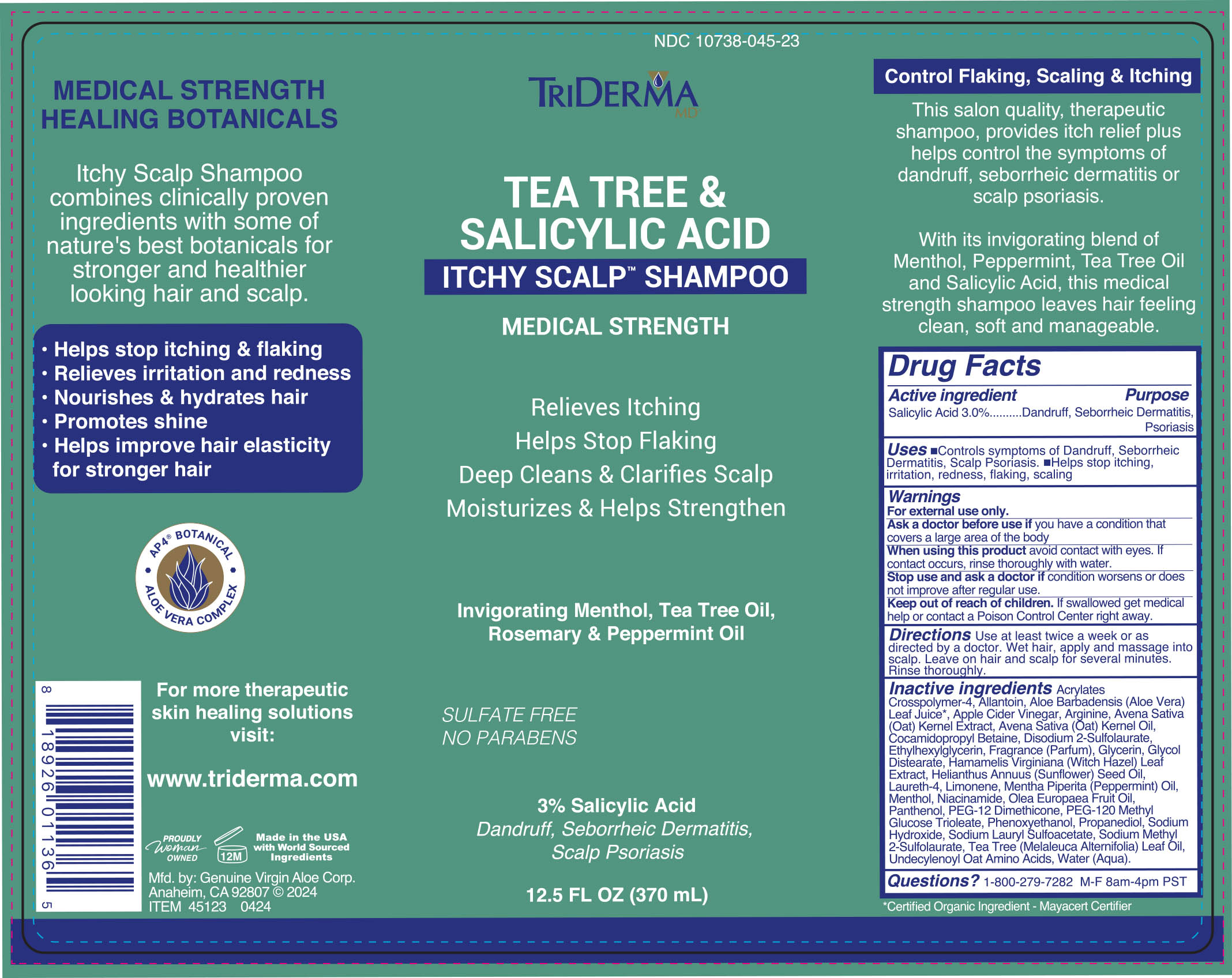 DRUG LABEL: TriDerma Itchy Scalp
NDC: 10738-045 | Form: SHAMPOO
Manufacturer: Genuine Virgin Aloe Corporation
Category: otc | Type: HUMAN OTC DRUG LABEL
Date: 20260129

ACTIVE INGREDIENTS: SALICYLIC ACID 3 g/100 g
INACTIVE INGREDIENTS: ALOE VERA LEAF JUICE; PANTHENOL; MELALEUCA ALTERNIFOLIA (TEA TREE) LEAF OIL; MENTHOL; ALLANTOIN

TriDerma Shampoo

ACTIVE INGREDIENT

Salicylic Acid 3.0%

PURPOSE

dandruff, seborrheic dermatitis, psoriasis

DOSAGE AND ADMINISTRATION

Directions Use at least twice a week or as directed by a doctor. Wet hair, apply and massage into scalp. Leave on for several minutes. Rinse thoroughly.

Keep out of reach of children. If swallowed get medical help or contact a Poison Control Center right away.

INDICATIONS AND USAGE

helps prevent symptoms of dandruff, seborrheic dermatitis, scalp psoriasis. Helps stop itching, irritation, redness, flaking, scaling:

When using this product •avoid contact with eyes. If contact occurs, rinse thoroughly with water.

Stop use and ask a doctor if •condition worsens or does not improve after regular use.

INACTIVE INGREDIENT

Acrylates Crosspolymer-4, Allantoin, Aloe Barbadensis (Aloe Vera) Leaf Juice*, Apple Cider Vinegar, Arginine, Avena Sativa (Oat) Kernel Extract, Avena Sativa (Oat) Kernel Oil, Cocamidopropyl Betaine, Disodium 2-Sulfolaurate, Ethylhexylglycerin, Fragrance (Parfum), Glycerin, Glycol Distearate, Hamamelis Virginiana (Witch Hazel) Leaf Extract, Helianthus Annuus (Sunflower) Seed Oil, Laureth-4, Limonene, Mentha Piperita (Peppermint) Oil, Menthol, Niacinamide, Olea Europaea Fruit Oil, Panthenol, PEG-12 Dimethicone, PEG-120 Methyl Glucose Trioleate, Phenoxyethanol, Propanediol, Sodium Hydroxide, Sodium Lauryl Sulfoacetate, Sodium Methyl 2-Sulfolaurate, Tea Tree (Melaleuca Alternifolia) Leaf Oil, Undecylenoyl Oat Amino Acids, Water (Aqua).

WARNINGS

Warnings For external use only. Ask a doctor before use if you have •psoriasis that covers a large area of the body. When using this product •avoid contact with eyes. If contact occurs, rinse thoroughly with water. Stop use and ask a doctor if •condition worsens or does not improve after regular use.